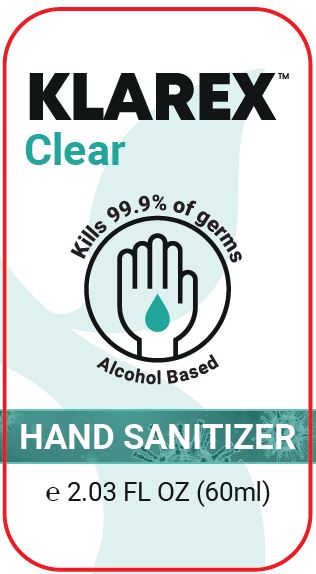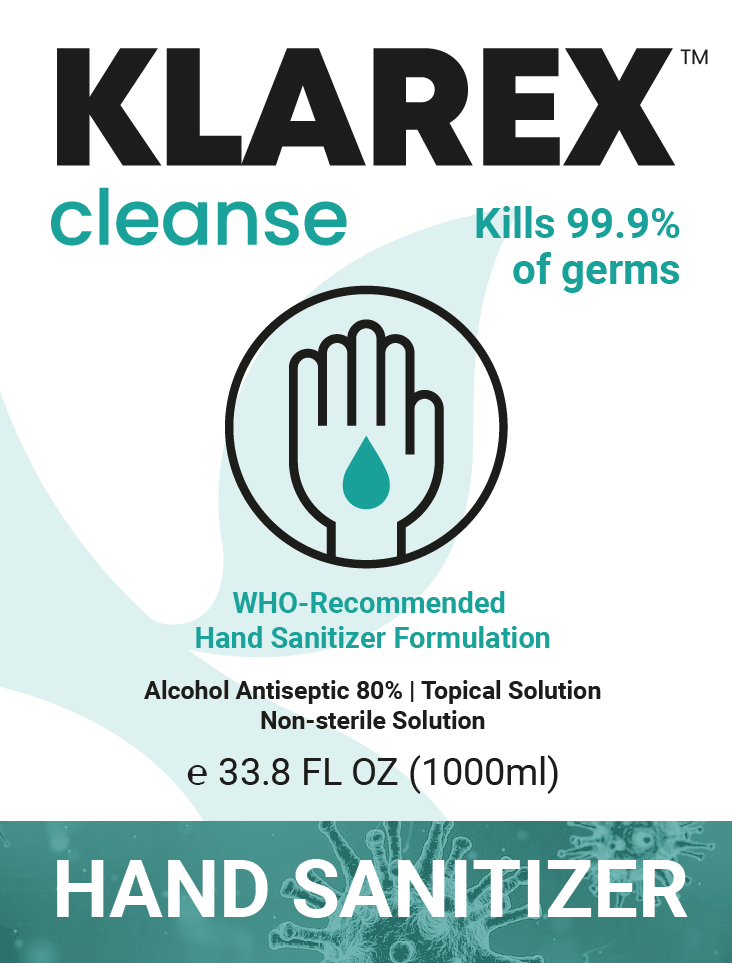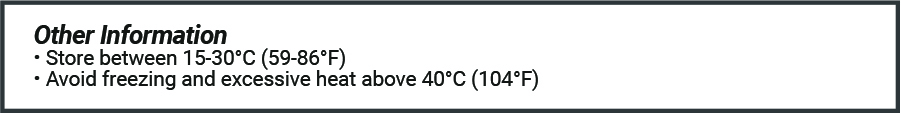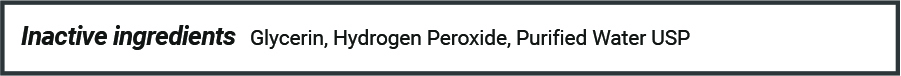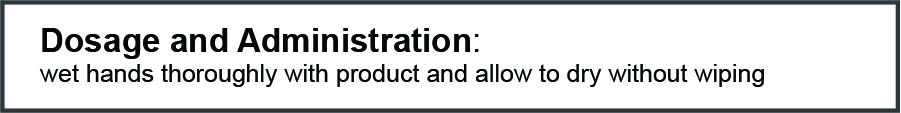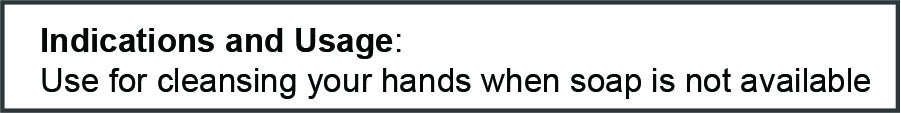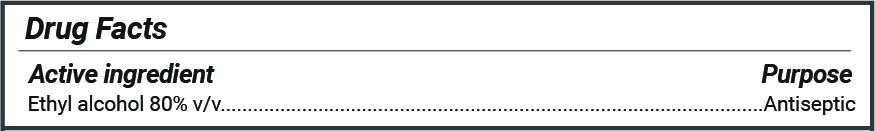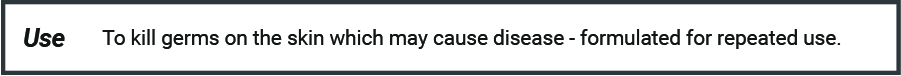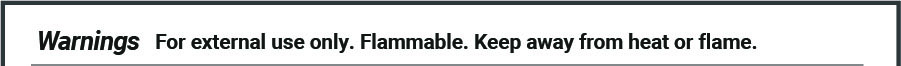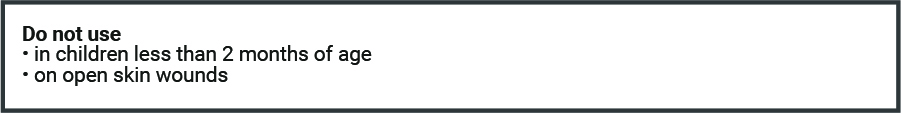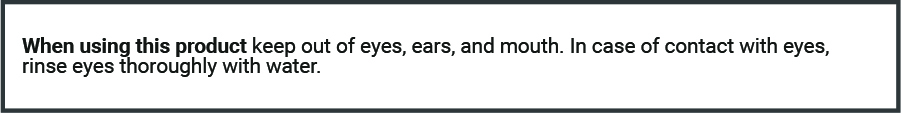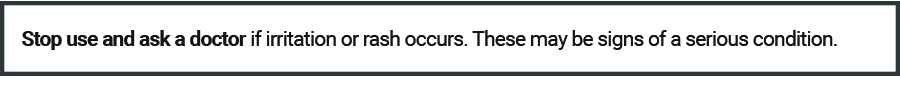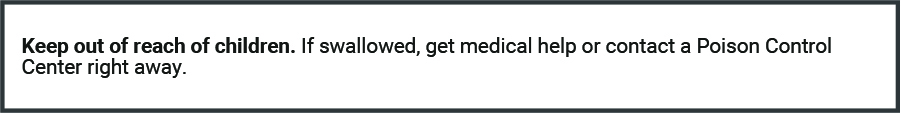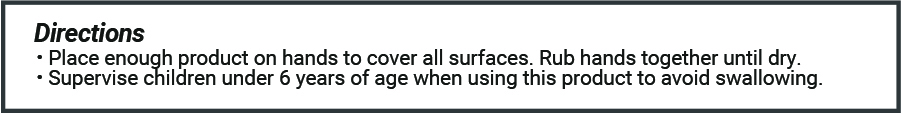 DRUG LABEL: Klarex Cleanse
NDC: 73753-821 | Form: SOLUTION
Manufacturer: HUNGARO-GAL KFT
Category: otc | Type: HUMAN OTC DRUG LABEL
Date: 20220117

ACTIVE INGREDIENTS: ALCOHOL 80 mL/100 mL
INACTIVE INGREDIENTS: WATER 18.425 mL/100 mL; GLYCERIN 1.45 mL/100 mL; HYDROGEN PEROXIDE 0.125 mL/100 mL

Drug Facts Active Ingredients

Drug Facts

Active ingredient

Ethyl Alcohol 80% v/v....................................

Prupose

Antiseptic

Use

Use to kill germs on the skin which may cause disease - formulated for repeated use

Warnings

Warnings For external use only. Flammable. Keep away from heat or flame.

Do not use * in children less than 2 month of age * on open skin wounds

When using this product keep out of eyes, ears, and mouth. In case of contact with eyes, rinse eyes thorouthly with water.

Stop use and ask a doctor if irritation or rash occurs. These may be signs of a serious condition.

Keep out of reach of children. If swallowed, get medical help or contact a Poison Control Center right away.

Directions

Directions * Place enough product on hands to cover all surfaces. Rub hands together until dry. * Supervise children under 6 years of age when using this product to avoid swallowing.

Other Information

* Store between 15-30OC (59-86OF)

* Avoid freezing and excessive heat above 40OC (104OF)

Inactive Ingredients

Inactive Ingredients glycerin, hydrogen peroxide, purified water USP

Indications and Usage

Indicatons and Usage: Use for cleansing your hands when soap is not available

Dosage and Administration: wet hands thoroughly with product and allow to dry without wiping

Principal Display Panel

KLAREX cleanse tm

Alcohol Antiseptic 80%

Topical Solution

Non-sterile Solution

e 33.8 FL OZ (1000ml)

Hand Sanitizer

who-recommended Hand Sanitizer Formulation

Kills 99.9% of germs

Klarex Clear Principal Display panel

Klarex Cler

Hand Sanitizer